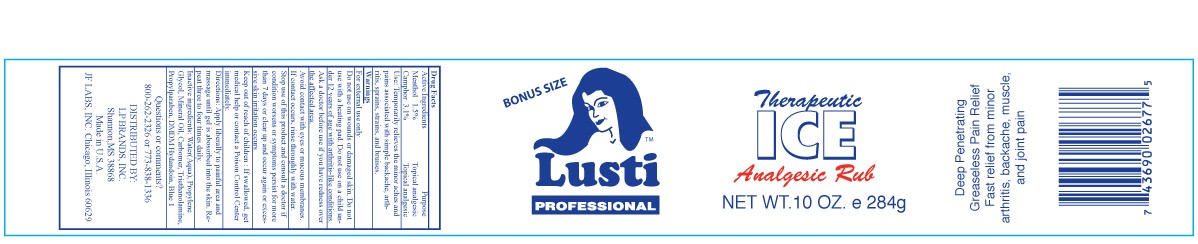 DRUG LABEL: Lusti Therapeutic Ice Analgesic Rub 
NDC: 49681-010 | Form: GEL
Manufacturer: New Life Products, Inc.
Category: otc | Type: HUMAN OTC DRUG LABEL
Date: 20230202

ACTIVE INGREDIENTS: MENTHOL, UNSPECIFIED FORM .015 g/1 g; CAMPHOR (SYNTHETIC) .031 g/1 g
INACTIVE INGREDIENTS: WATER; PROPYLENE GLYCOL; MINERAL OIL; CARBOMER HOMOPOLYMER TYPE B (ALLYL SUCROSE CROSSLINKED); TROLAMINE; METHYLPARABEN; PROPYLPARABEN; DMDM HYDANTOIN; FD&C BLUE NO. 1

Lusti Therapeutic Ice Analgesic Rub

OTC - ACTIVE INGREDIENT SECTION

Menthol 1.5% Camphor 3.1%

OTC - PURPOSE SECTION

Topical Analgesic. Temporarily relieves the minor aches and paiins associated with simple backache, arthritis, sprains, strains and bruises.

Use:

Temporarily relieves the minor aches and pains associated with simple backache, arthritis, sprains, and bruises.

WARNINGS SECTION

For external use only

OTC - DO NOT USE SECTION

Do not use on wounds or damaged skin. Do not use with a heating pad. Do not use on a child under 12 years of age with arthritis-like conditions.

OTC - ASK DOCTOR SECTION

Ask a doctor before use if you have redness over the affected area.

OTC - WHEN USING SECTION

Avoid contact with eyes or mucous membranes. If contact occurs, rinse thoroughly with water.

OTC - STOP USE SECTION

Stop use of this product and consult a doctor if condition worsens or symptoms persist for more than 7 days or clear up and occur again or excessive skin irritation occurs.

OTC - KEEP OUT OF REACH OF CHILDREN SECTION

Keep out of reach of children. If swallowed, get medical help or contact a Poison Control Center immediately.

DIRECTIONS SECTION

Apply liberally to painful area and massage until gel is absorbed into the skin. Repeat three to four times daily.

INACTIVE INGREDIENT SECTION

Inactive ingredients: Water (Aqua), Propylene Glycol, Mineral Oil, Carbomer, Triethanolamine, Methylparaben, Propylparaben, DMDM Hydantoin, Blue 1

OTC - QUESTIONS SECTION

Questions or comments: www.jflabs.comJF LABS, INC. Chicago, Illinois 60629

PACKAGE LABEL.

BONUS SIZE

Lusti

PROFESSIONAL

Therapeutic ICE

Analgesic Rub

NET WT. 10 OZ. e 284g

Deep Penetrating

Greaseless Pain Relief

Fast relief from minor

arthritis, backache, muscle,

and joint pain